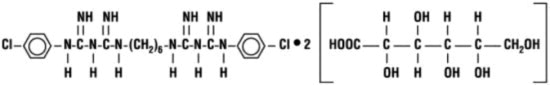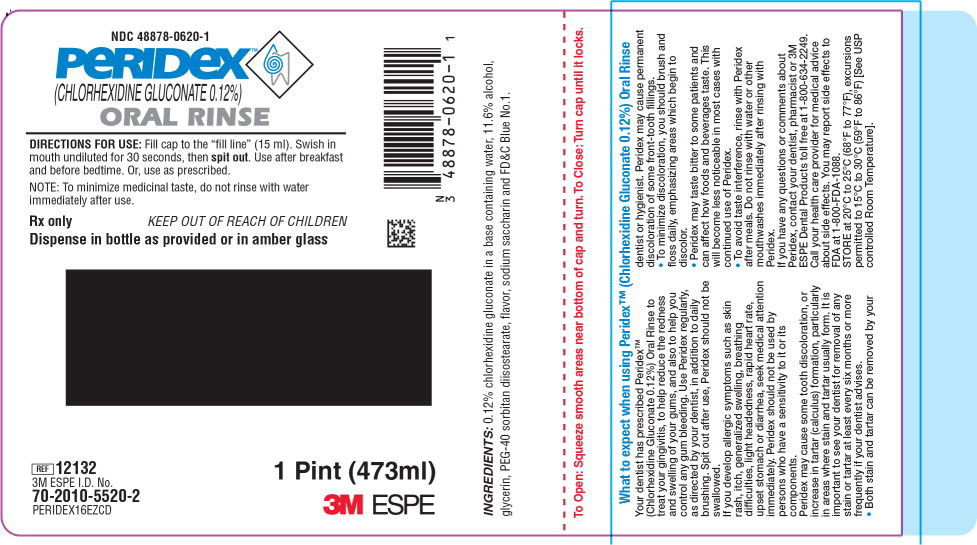 DRUG LABEL: Peridex
NDC: 48878-0620 | Form: RINSE
Manufacturer: Solventum US LLC
Category: prescription | Type: HUMAN PRESCRIPTION DRUG LABEL
Date: 20240801

ACTIVE INGREDIENTS: Chlorhexidine Gluconate 1.2 mg/1 mL
INACTIVE INGREDIENTS: Glycerin; Saccharin Sodium; FD&C BLUE NO. 1; Water; Alcohol

PERIDEX™
(CHLORHEXIDINE GLUCONATE 0.12%)
ORAL
RINSE
NDC 48878-0620-1

DESCRIPTION:

Peridex™ (Chlorhexidine Gluconate 0.12%) Oral Rinse is an oral rinse containing 0.12% chlorhexidine gluconate (1, 1^1-hexamethylene bis [5-(p-chlorophenyl) biguanide] di-D-gluconate) in a base containing water, 11.6% alcohol, glycerin, PEG-40 sorbitan diisostearate, flavor, sodium saccharin, and FD&C Blue No. 1. Peridex is a near-neutral solution (pH range 5-7). Chlorhexidine gluconate is a salt of chlorhexidine and gluconic acid. Its chemical structure is:

CLINICAL PHARMACOLOGY:

Peridex™ (Chlorhexidine Gluconate 0.12%) Oral Rinse provides antimicrobial activity during oral rinsing. The clinical significance of Peridex oral rinse's antimicrobial activities is not clear. Microbiological sampling of plaque has shown a general reduction of counts of certain assayed bacteria, both aerobic and anaerobic, ranging from 54-97% through six months use. Use of Peridex in a six month clinical study did not result in any significant changes in bacteria resistance, overgrowth of potentially opportunistic organisms or other adverse changes in the oral microbial ecosystem. Three months after Peridex use was discontinued, the number of bacteria in plaque had returned to baseline levels and resistance of plaque bacteria to chlorhexidine gluconate was equal to that at baseline.

PHARMACOKINETICS:

Pharmacokinetic studies with Peridex indicate approximately 30% of the active ingredient, chlorhexidine gluconate, is retained in the oral cavity following rinsing. This retained drug is slowly released into the oral fluids. Studies conducted on human subjects and animals demonstrate chlorhexidine gluconate is poorly absorbed from the gastrointestinal tract. The mean plasma level of chlorhexidine gluconate reached a peak of 0.206 mcg/g in humans 30 minutes after they ingested a 300mg dose of the drug. Detectable levels of chlorhexidine gluconate were not present in the plasma of these subjects 12 hours after the compound was administered. Excretion of chlorhexidine gluconate occurred primarily through the feces (~90%). Less than 1% of the chlorhexidine gluconate ingested by these subjects was excreted in the urine.

INDICATION:

Peridex is indicated for use between dental visits as part of a professional program for the treatment of gingivitis as characterized by redness and swelling of the gingivae, including gingival bleeding upon probing. Peridex has not been tested among patients with acute necrotizing ulcerative gingivitis (ANUG). For patients having coexisting gingivitis and periodontitis, see PRECAUTIONS.

CONTRAINDICATIONS:

Peridex should not be used by persons who are known to be hypersensitive to chlorhexidine gluconate or other formula ingredients.

WARNINGS:

The effect of Peridex on periodontitis has not been determined. An increase in supragingival calculus was noted in clinical testing in Peridex users compared with control users. It is not known if Peridex use results in an increase in subgingival calculus. Calculus deposits should be removed by a dental prophylaxis at intervals not greater than six months.

Anaphylaxis, as well as serious allergic reactions, have been reported during postmarketing use with dental products containing chlorhexidine.

SEE CONTRAINDICATIONS.

PRECAUTIONS:

General:

1. For patients having coexisting gingivitis and periodontitis, the presence or absence of gingival inflammation following treatment with Peridex should not be used as a major indicator of underlying periodontitis.
2. Peridex can cause staining of oral surfaces, such as tooth surfaces, restorations, and the dorsum of the tongue. Not all patients will experience a visually significant increase in toothstaining. In clinical testing, 56% of Peridex users exhibited a measurable increase in facial anterior stain, compared to 35% of control users after six months; 15% of Peridex users developed what was judged to be heavy stain, compared to 1% of control users after six months. Stain will be more pronounced in patients who have heavier accumulations of unremoved plaque. Stain resulting from use of Peridex does not adversely affect health of the gingivae or other oral tissues. Stain can be removed from most tooth surfaces by conventional professional prophylactic techniques. Additional time may be required to complete the prophylaxis. Discretion should be used when prescribing to patients with anterior facial restorations with rough surfaces or margins. If natural stain cannot be removed from these surfaces by a dental prophylaxis, patients should be excluded from Peridex treatment if permanent discoloration is unacceptable. Stain in these areas may be difficult to remove by dental prophylaxis and on rare occasions may necessitate replacement of these restorations.
3. Some patients may experience an alteration in taste perception while undergoing treatment with Peridex. Rare instances of permanent taste alteration following Peridex use have been reported via post-marketing product surveillance.

PREGNANCY

Pregnancy: Teratogenic Effects. Reproduction studies have been performed in rats and rabbits at chlorhexidine gluconate doses up to 300mg/kg/day and 40mg/kg/day, respectively, and have not revealed evidence of harm to fetus. However, adequate and well-controlled studies in pregnant women have not been done. Because animal reproduction studies are not always predictive of human response, this drug should be used during pregnancy only if clearly needed.

NURSING MOTHERS

Nursing Mothers: It is not known whether this drug is excreted in human milk. Because many drugs are excreted in human milk, caution should be exercised when Peridex is administered to nursing women. In parturition and lactation studies with rats, no evidence of impaired parturition or of toxic effects to suckling pups was observed when chlorhexidine gluconate was administered to dams at doses that were over 100 times greater than that which would result from a person's ingesting 30ml (2 capfuls) of Peridex per day.

PEDIATRIC USE

Pediatric Use: Clinical effectiveness and safety of Peridex™ (Chlorhexidine Gluconate 0.12%) Oral Rinse have not been established in children under the age of 18.

CARCINOGENESIS AND MUTAGENESIS AND IMPAIRMENT OF FERTILITY

Carcinogenesis, Mutagenesis, and Impairment of Fertility: In a drinking water study in rats, carcinogenic effects were not observed at doses up to 38mg/kg/day. Mutagenic effects were not observed in two mammalian in vivo mutagenesis studies with chlorhexidine gluconate. The highest doses of chlorhexidine used in a mouse dominant-lethal assay and a hamster cytogenetics test were 1000mg/kg/day and 250mg/kg/day, respectively. No evidence of impaired fertility was observed in rats at doses up to 100mg/kg/day.

ADVERSE REACTIONS:

The most common side effects associated with chlorhexidine gluconate oral rinses are: 1) an increase in staining of teeth and other oral surfaces; 2) an increase in calculus formation; and 3) an alteration in taste perception, see WARNINGS and PRECAUTIONS. Oral irritation and local allergy-type symptoms have been spontaneously reported as side effects associated with use of chlorhexidine gluconate rinse. The following oral mucosal side effects were reported during placebo-controlled adult clinical trials: aphthous ulcer, grossly obvious gingivitis, trauma, ulceration, erythema, desquamation, coated tongue, keratinization, geographic tongue, mucocele, and short frenum. Each occurred at a frequency of less than 1%. Among post marketing reports, the most frequently reported oral mucosal symptoms associated with Peridex are stomatitis, gingivitis, glossitis, ulcer, dry mouth, hypesthesia, glossal edema, and paresthesia. Minor irritation and superficial desquamation of the oral mucosa have been noted in patients using Peridex. There have been cases of parotid gland swelling and inflammation of the salivary glands (sialadenitis) reported in patients using Peridex.

OVERDOSAGE:

Ingestion of 1 or 2 ounces of Peridex by a small child (~1O kg body weight) might result in gastric distress, including nausea, or signs of alcohol intoxication. Medical attention should be sought if more than 4 ounces of Peridex is ingested by a small child or if signs of alcohol intoxication develop.

DOSAGE AND ADMINISTRATION:

Peridex therapy should be initiated directly following a dental prophylaxis. Patients using Peridex should be reevaluated and given a thorough prophylaxis at intervals no longer than six months. Recommended use is twice daily oral rinsing for 30 seconds, morning and evening after toothbrushing. Usual dosage is 15ml (marked in cap) of undiluted Peridex. Patients should be instructed to not rinse with water or other mouthwashes, brush teeth or eat immediately after using Peridex. Peridex is not intended for ingestion and should be expectorated after rinsing.

HOW SUPPLIED:

Peridex is supplied as a blue liquid in 4-ounce (118ml), 1-pint (473ml) and 64-ounce (1893ml) white or amber plastic bottles with child-resistant dispensing closures.

STORAGE AND HANDLING

STORE at 20°C to 25°C (68°F to 77°F), excursions permitted to 15°C to 30°C (59°F to 86°F)

[See USP controlled Room Temperature].

Rx only

Keep out of reach of children

Revised: July 2022

Made in U.S.A. for:
3M ESPE Dental Products
2510 Conway Avenue
St. Paul, MN 55144-1000 USA

©3M 2022

Principal Display Panel - Peridex Bottle Label

NDC 48878-0620-1

PERIDEX™

(CHLORHEXIDINE GLUCONATE 0.12%)

ORAL RINSE

DIRECTIONS FOR USE: Fill cap to the “fill line” (15 ml). Swish in

mouth undiluted for 30 seconds, then spit out. Use after breakfast

and before bedtime. Or, use as prescribed.

NOTE: To minimize medicinal taste, do not rinse with water

immediately after use.

Rx only

KEEP OUT OF REACH OF CHILDREN

Dispense in bottle as provided or in amber glass

REF 12132

3M ESPE I.D. No.

70-2010-5520-2

PERIDEX16EZCD

1 Pint (473ml)

3M ESPE

INGREDIENTS: 0.12% chlorhexidine gluconate in a base containing water, 11.6% alcohol,

glycerin, PEG-40 sorbitan diisostearate, flavor, sodium saccharin and FD&C Blue No.1.

To Open: Squeeze smooth areas near bottom of cap and turn. To Close: Turn cap until it locks.

What to expect when using Peridex™ (Chlorhexidine Gluconate 0.12%) Oral Rinse

Your dentist has prescribed Peridex™

(Chlorhexidine Gluconate 0.12%) Oral Rinse to

treat your gingivitis, to help reduce the redness

and swelling of your gums, and also to help you

control any gum bleeding. Use Peridex regularly,

as directed by your dentist, in addition to daily

brushing. Spit out after use, Peridex should not be

swallowed.

If you develop allergic symptoms such as skin

rash, itch, generalized swelling, breathing

difficulties, light headedness, rapid heart rate,

upset stomach or diarrhea, seek medical attention

immediately. Peridex should not be used by

persons who have a sensitivity to it or its

components.

Peridex may cause some tooth discoloration, or

increase in tartar (calculus) formation, particularly

in areas where stain and tartar usually form. It is

important to see your dentist for removal of any

stain or tartar at least every six months or more

frequently if your dentist advises.

• Both stain and tartar can be removed by your

dentist or hygienist. Peridex may cause permanent

discoloration of some front-tooth fillings.

• To minimize discoloration, you should brush and

floss daily, emphasizing areas which begin to

discolor.

• Peridex may taste bitter to some patients and

can affect how foods and beverages taste. This

will become less noticeable in most cases with

continued use of Peridex.

• To avoid taste interference, rinse with Peridex

after meals. Do not rinse with water or other

mouthwashes immediately after rinsing with

Peridex.

If you have any questions or comments about

Peridex, contact your dentist, pharmacist or 3M

ESPE Dental Products toll free at 1-800-634-2249.

Call your health care provider for medical advice

about side effects. You may report side effects to

FDA at 1-800-FDA-1088.

STORE at 20°C to 25°C (68°F to 77°F), excursions

permitted to 15°C to 30°C (59°F to 86°F) [See USP

controlled Room Temperature].

INCIRC™